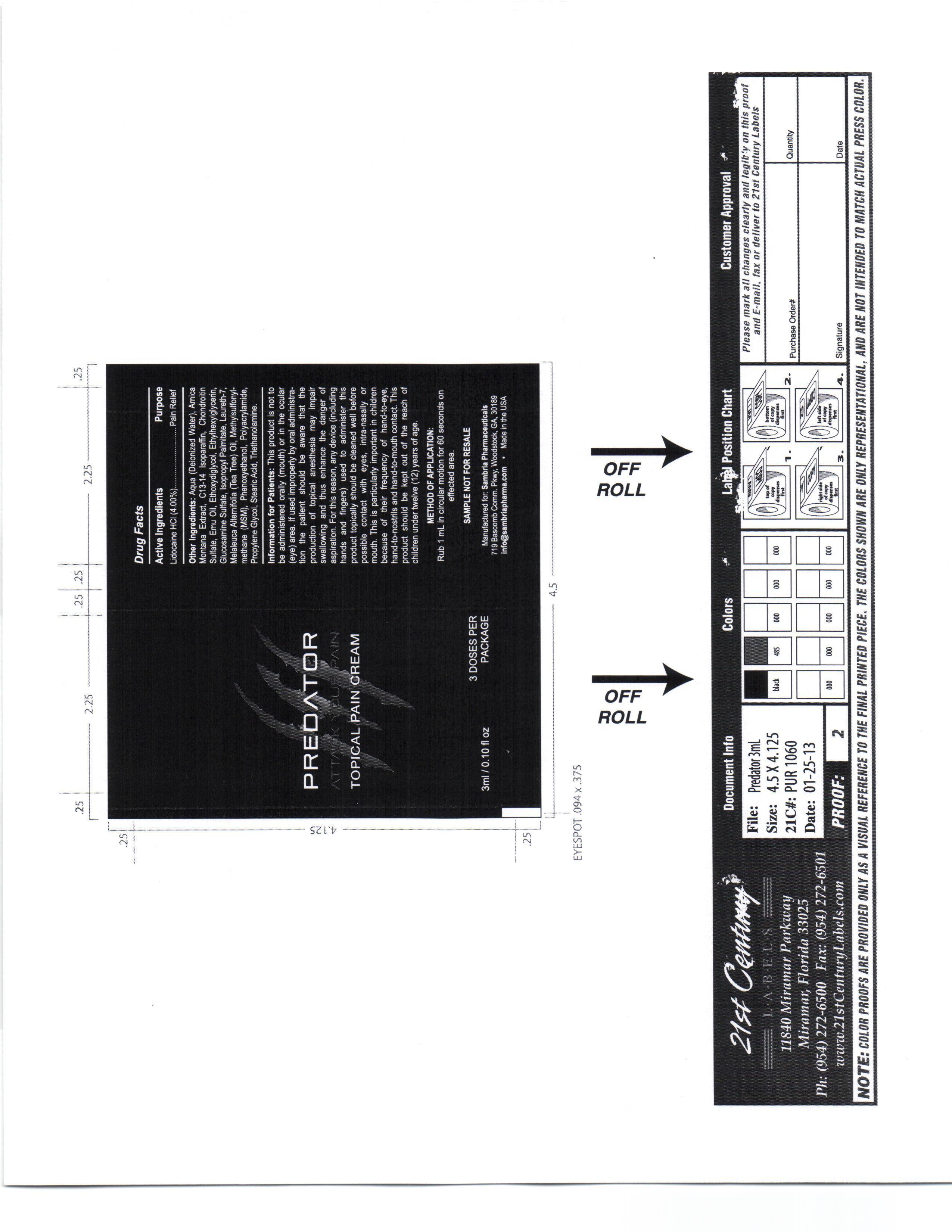 DRUG LABEL: Predator
NDC: 54723-150 | Form: CREAM
Manufacturer: Sambria Pharmaceuticals, LLC
Category: otc | Type: HUMAN OTC DRUG LABEL
Date: 20130225

ACTIVE INGREDIENTS: LIDOCAINE HYDROCHLORIDE 400 mg/1 mg
INACTIVE INGREDIENTS: WATER; ARNICA MONTANA FLOWER; C13-14 ISOPARAFFIN; CHONDROITIN SULFATE (BOVINE); EMU OIL; DIETHYLENE GLYCOL MONOETHYL ETHER; ETHYLHEXYLGLYCERIN; GLUCOSAMINE SULFATE; ISOPROPYL PALMITATE; LAURETH-7; TEA TREE OIL; DIMETHYL SULFONE; PHENOXYETHANOL; POLYACRYLAMIDE (10000 MW); PROPYLENE GLYCOL; STEARIC ACID; TRIETHANOLAMINE BENZOATE

Predator

Information for Patients

This product is not to be administered orally (mouth) or in the ocular (eye) area.

If used improperly by oral administration the patient should be aware that the production of topical anesthesia may impair swallowing and thus enhance the danger of aspiration. For this reason, any device (including hands and fingers) used to administer this product topically should be cleaned well before possible contact with eyes, intra-nasaly or mouth.

active ingredients

lidocaine HCL 4%

Other ingredients

Aqua, Amica Montana Extract, C13-14 Isoparafin, Chondrotin Sulfate, Emu Oil, Ethoxydiglycol, Ethylhexylglycerin, Glucosamine Sulfate, Isopropyl Palmitate, Laureth 7, Melaleuca Alternifoil (Tea Tree) oil, Methylsulfonylmethana (MSM), Phenoxyethanol, Polyacrylamide, Propylene Glycol, Stearic Acid, Triethanolamine

KEEP OUT OF REACH OF CHILDREN

This product should be kept out of the reach of children uner twelve (12) years of age.

PURPOSE

Pain relief

Method of Application

Rub 1ml in circular motion for 6 0seconds on effected area.

DOSAGE AND ADMINISTRATION

Rub 1ml in cicular motion for 60 seconds on effected area.